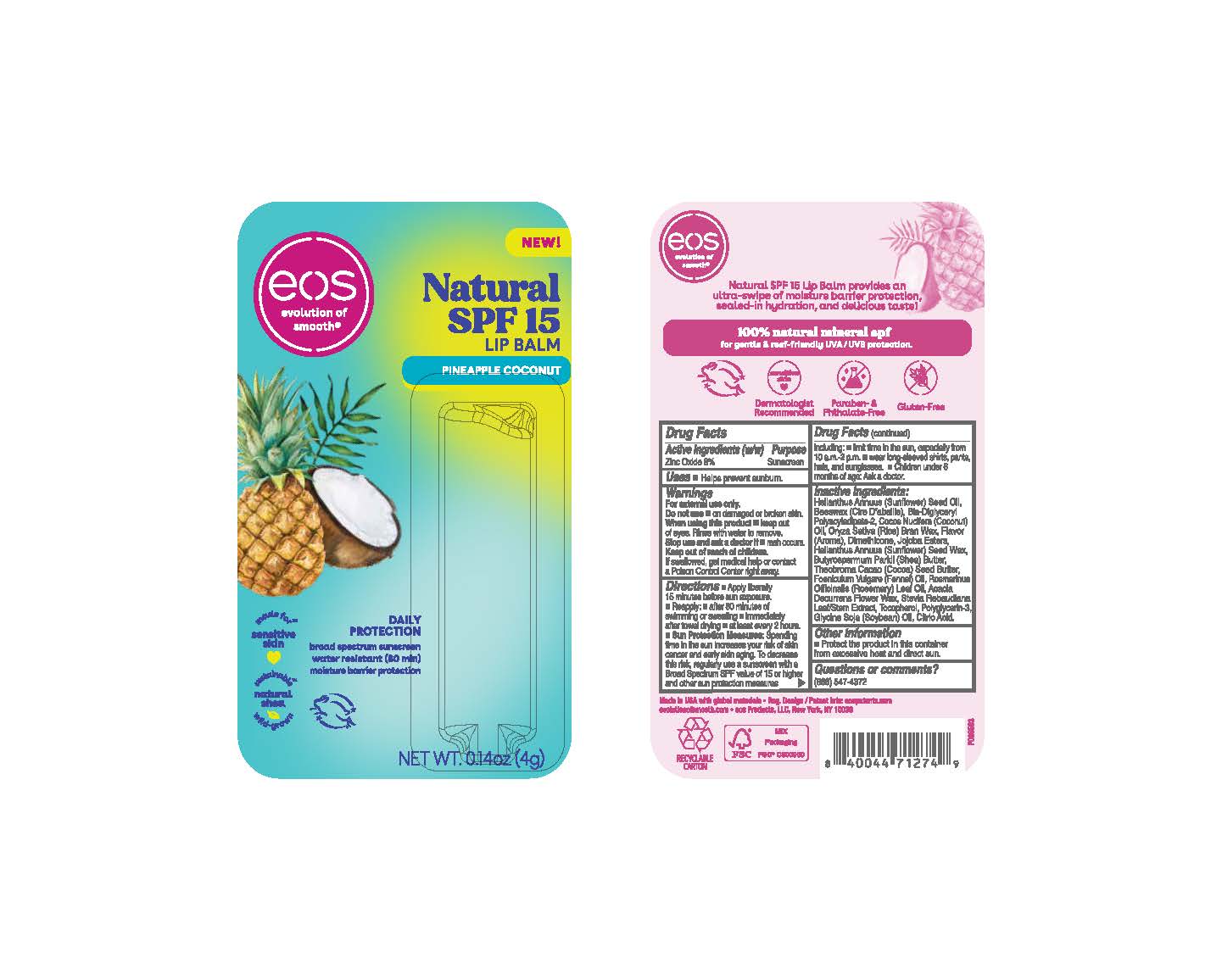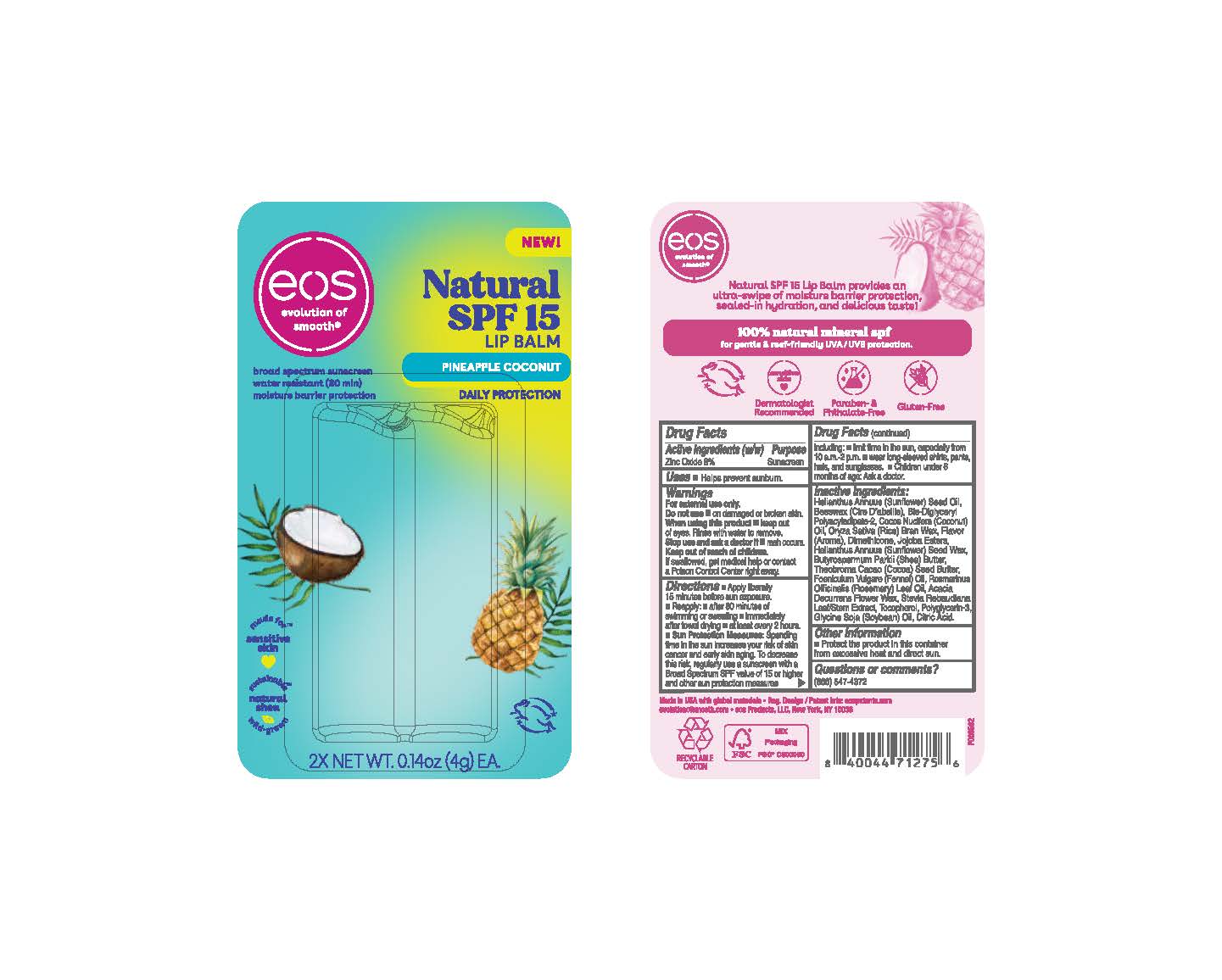 DRUG LABEL: eos Natural SPF 15 Lip Balm
NDC: 70170-0022 | Form: STICK
Manufacturer: eos Products LLC
Category: otc | Type: HUMAN OTC DRUG LABEL
Date: 20230823

ACTIVE INGREDIENTS: ZINC OXIDE 0.32 g/4 g
INACTIVE INGREDIENTS: YELLOW WAX; JOJOBA OIL; HELIANTHUS ANNUUS SEED WAX; ACACIA DECURRENS FLOWER WAX; STEVIA REBAUDIUNA LEAF; ROSEMARY OIL; COCONUT OIL; POLYGLYCERIN-3; RICE BRAN; BIS-DIGLYCERYL POLYACYLADIPATE-2; SUNFLOWER OIL; TOCOPHEROL; COCOA BUTTER; SHEA BUTTER; FENNEL OIL; SOYBEAN OIL; CITRIC ACID MONOHYDRATE; DIMETHICONE

eos Natural SPF 15 Lip Balm

Drug Facts

Active Ingredients Purpose

Zinc Oxide 8% Sunscreen

Uses

- Helps prevent sunburn.

WARNINGS

For external use only.

Do not use • on damaged or broken skin.

When using this product • keep out of eyes. Rinse with water to remove.

Stop use and ask a doctor if • rash occurs.

Keep out of reach of children. If swallowed, get medical help or contact a Poison Control Center right away.

Directions

- Apply liberally 15 minutes before sun exposure.
- Reapply:

- after 80 minutes of swimming or sweating

- immediately after towel drying

- at least every 2 hours

- Sun Protection Measures: Spending time in the sun increases your risk of skin cancer and early skin aging. To decrease this risk, regularly use a sunscreen with a Broad Spectrum SPF value of 15 or higher and other sun protection measures, including:

- Limit time in the sun, especially from 10 a.m.-2 p.m.

- Wear long-sleeved shirts, pants, hats, and sunglasses.

- Children under 6 months of age: Ask a doctor.

Inactive Ingredients:

Helianthus annuus (Sunflower) Seed Oil, Beeswax (Cire D'abeille), Bis-Diglyceryl Polyacylapidate-2, Cocos Nucifera (Coconut) Oil, Oryza Sativa (Rice) Bran Wax, Flavor (Aroma), Dimethicone, Jojoba Esters, Helianthus annuus (Sunflower) Seed Wax, Butyrospermum Parkii (Shea) Butter, Theobroma Cacao (Cocoa) Seed Butter, Foeniculum Vulgare (Fennel) Oil, Rosemarinus Officinalis (Rosemary) Leaf Oil, Acacia Decurrens Flower Wax, Stevia Rebaudiana Leaf/Stem Extract, Tocopherol, Polyglycerin-3, Glycine Soja (Soyabean) Oil, Citric Acid.

Other Information

- Protect the product in this container from excessive heat and direct sun.

Questions or comments?

(866) 547-4372

Principal Display Panel 0.14 o.z. (4g)

eos Natural SPF 15 Lip Balm 0.14 o.z. (4g)

Principal Display Panel 2 X 0.14 o.z. (4g)

2 X eos Natural SPF 15 Lip Balm 0.14 o.z. (4g)